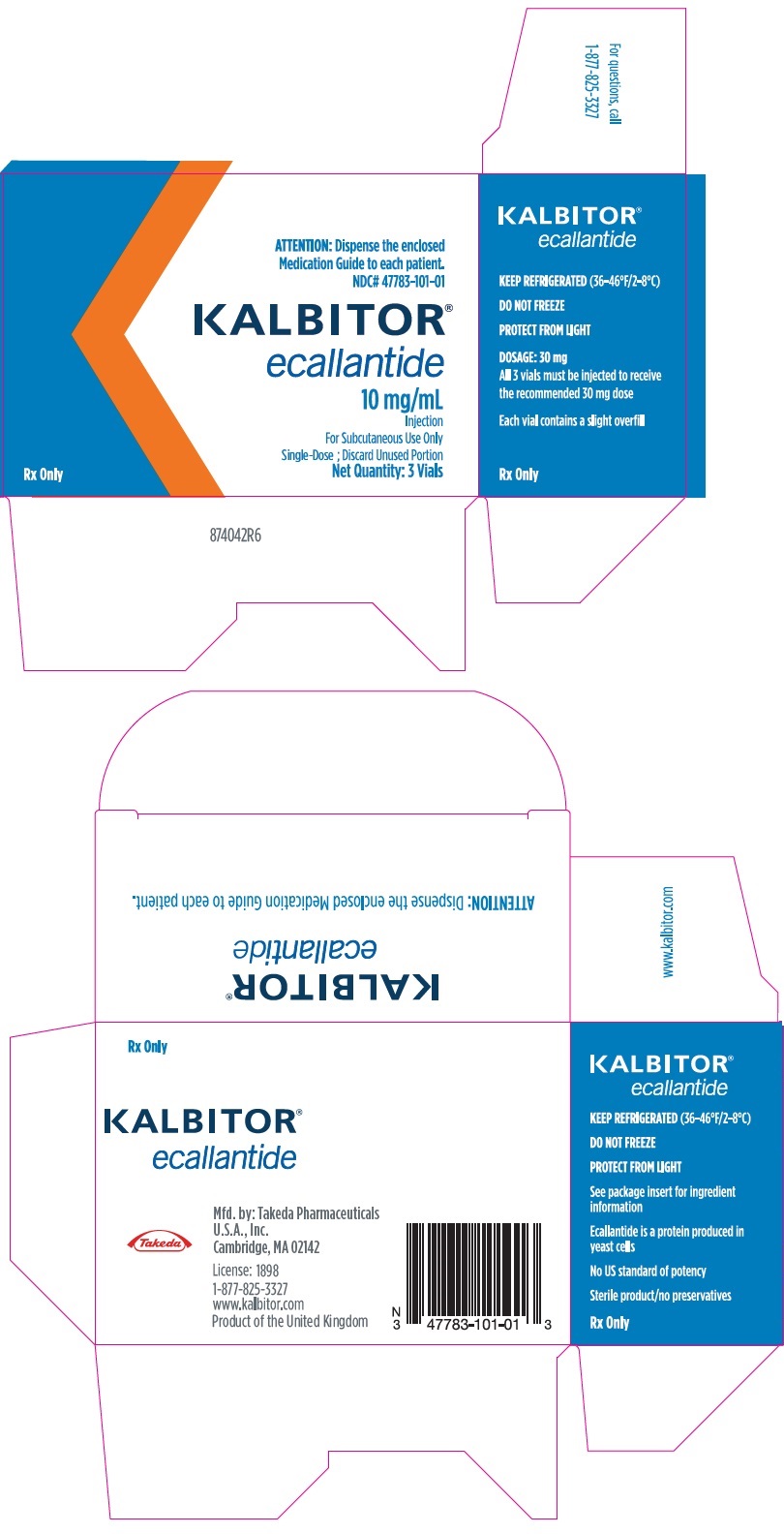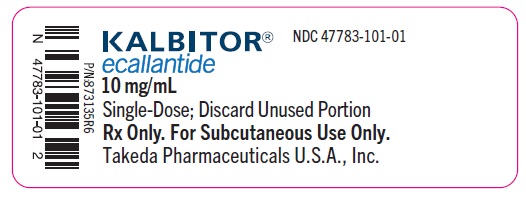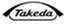 DRUG LABEL: Kalbitor
NDC: 47783-101 | Form: INJECTION, SOLUTION
Manufacturer: Takeda Pharmaceuticals America, Inc.
Category: prescription | Type: HUMAN PRESCRIPTION DRUG LABEL
Date: 20250701

ACTIVE INGREDIENTS: Ecallantide 10 mg/1 mL
INACTIVE INGREDIENTS: SODIUM PHOSPHATE, DIBASIC, DIHYDRATE 0.76 mg/1 mL; Monobasic Potassium Phosphate 0.2 mg/1 mL; Potassium Chloride 0.2 mg/1 mL; Sodium Chloride 8 mg/1 mL

HIGHLIGHTS OF PRESCRIBING INFORMATION

These highlights do not include all the information needed to use KALBITOR® safely and effectively. See full prescribing information for KALBITOR.
KALBITOR (ecallantide) injection, for subcutaneous use
Initial U.S. Approval: 2009

WARNING: ANAPHYLAXIS

See full prescribing information for complete boxed warning

Anaphylaxis has been reported after administration of KALBITOR®. Because of the risk of anaphylaxis, KALBITOR should only be administered by a healthcare professional with appropriate medical support to manage anaphylaxis and hereditary angioedema. Healthcare professionals should be aware of the similarity of symptoms between hypersensitivity reactions and hereditary angioedema and patients should be monitored closely. Do not administer KALBITOR to patients with known clinical hypersensitivity to KALBITOR [see Contraindications (4), Warnings and Precautions (5.1), and Adverse Reactions (6)].

1 INDICATIONS AND USAGE

KALBITOR is a plasma kallikrein inhibitor indicated for treatment of acute attacks of hereditary angioedema (HAE) in patients 12 years of age and older. (1)

2 DOSAGE AND ADMINISTRATION

- 30 mg (3 mL), administered subcutaneously in three 10 mg (1 mL) injections. If an attack persists, an additional dose of 30 mg may be administered within a 24 hour period. (2.1)
- KALBITOR should only be administered by a healthcare professional with appropriate medical support to manage anaphylaxis and hereditary angioedema. (2.2).

3 DOSAGE FORMS AND STRENGTHS

Single-dose glass vial containing 10 mg/mL of ecallantide as a solution for injection. (3)

4 CONTRAINDICATIONS

Do not administer KALBITOR to a patient who has known clinical hypersensitivity to KALBITOR. (4)

5 WARNINGS AND PRECAUTIONS

Hypersensitivity Reactions Including Anaphylaxis: Anaphylaxis has occurred in 4% of treated patients. Administer KALBITOR in a setting equipped to manage anaphylaxis and hereditary angioedema. Given the similarity in hypersensitivity symptoms and acute HAE symptoms, monitor patients closely for hypersensitivity reactions (5).

6 ADVERSE REACTIONS

The most common adverse reactions occurring in ≥3% of KALBITOR-treated patients and greater than placebo are headache, nausea, diarrhea, pyrexia, injection site reactions, and nasopharyngitis. (6)

To report SUSPECTED ADVERSE REACTIONS, contact Takeda Pharmaceuticals U.S.A., Inc. at 1-877-TAKEDA-7 (1-877-825-3327) or FDA at 1-800-FDA-1088 or www.fda.gov/medwatch.

FULL PRESCRIBING INFORMATION

WARNING: ANAPHYLAXIS

Anaphylaxis has been reported after administration of KALBITOR. Because of the risk of anaphylaxis, KALBITOR should only be administered by a healthcare professional with appropriate medical support to manage anaphylaxis and hereditary angioedema. Healthcare professionals should be aware of the similarity of symptoms between hypersensitivity reactions and hereditary angioedema and patients should be monitored closely. Do not administer KALBITOR to patients with known clinical hypersensitivity to KALBITOR. [see Contraindications (4), Warnings and Precautions (5.1), and Adverse Reactions (6)]

1 INDICATIONS AND USAGE

KALBITOR® (ecallantide) is indicated for treatment of acute attacks of hereditary angioedema (HAE) in patients 12 years of age and older.

2 DOSAGE AND ADMINISTRATION

2.1 Recommended Dosing

The recommended dose of KALBITOR is 30 mg (3 mL), administered subcutaneously in three 10 mg (1 mL) injections. If the attack persists, an additional dose of 30 mg may be administered within a 24 hour period.

2.2 Administration Instructions

KALBITOR should only be administered by a healthcare professional with appropriate medical support to manage anaphylaxis and hereditary angioedema.

KALBITOR should be refrigerated and protected from the light. KALBITOR is a clear, colorless liquid; visually inspect each vial for particulate matter and discoloration prior to administration. If there is particulate matter or discoloration, the vial should not be used.

Using aseptic technique, withdraw 1 mL (10 mg) of KALBITOR from the vial using a large bore needle. Change the needle on the syringe to a needle suitable for subcutaneous injection. The recommended needle size is 27 gauge. Inject KALBITOR into the skin of the abdomen, thigh, or upper arm. Repeat the procedure for each of the 3 vials comprising the KALBITOR dose. The injection site for each of the injections may be in the same or in different anatomic locations (abdomen, thigh, upper arm). There is no need for site rotation. Injection sites should be separated by at least 2 inches (5 cm) and away from the anatomical site of attack.

The same instructions apply to an additional dose administered within 24 hours. Different injection sites or the same anatomical location (as used for the first administration) may be used.

3 DOSAGE FORMS AND STRENGTHS

KALBITOR is a clear, colorless liquid free of preservatives. Each vial of KALBITOR contains ecallantide at a concentration of 10 mg/mL.

4 CONTRAINDICATIONS

Do not administer KALBITOR to a patient who has known clinical hypersensitivity to KALBITOR. [see Warnings and Precautions (5.1)].

5 WARNINGS AND PRECAUTIONS

5.1 Hypersensitivity Reactions, Including Anaphylaxis

Potentially serious hypersensitivity reactions, including anaphylaxis, have occurred in patients treated with KALBITOR. In 255 HAE patients treated with intravenous or subcutaneous KALBITOR in clinical studies, 10 patients (4%) experienced anaphylaxis. For the subgroup of 187 patients treated with subcutaneous KALBITOR, 5 patients (3%) experienced anaphylaxis. Symptoms associated with these reactions have included chest discomfort, flushing, pharyngeal edema, pruritus, rhinorrhea, sneezing, nasal congestion, throat irritation, urticaria, wheezing, and hypotension. These reactions occurred within the first hour after dosing.

Other adverse reactions indicative of hypersensitivity reactions included the following: pruritus (5%), rash (3%), and urticaria (2%).

Patients should be observed for an appropriate period of time after administration of KALBITOR, taking into account the time to onset of anaphylaxis seen in clinical trials. Given the similarity in hypersensitivity symptoms and acute HAE symptoms, patients should be monitored closely in the event of a hypersensitivity reaction.

KALBITOR should not be administered to any patients with known clinical hypersensitivity to KALBITOR [see Contraindications (4)].

6 ADVERSE REACTIONS

Hypersensitivity reactions, including anaphylaxis, have occurred in patients treated with KALBITOR [see Contraindications (4) and Warnings and Precautions (5.1)].

6.1 Clinical Trials Experience

Because clinical trials are conducted under widely varying conditions, adverse reaction rates observed in the clinical trials of a drug cannot be directly compared to rates in the clinical trials of another drug and may not reflect the rates observed in practice.

The safety data described below reflect exposure to KALBITOR in 255 patients with HAE treated with either intravenous or subcutaneous KALBITOR. Of the 255 patients, 66% of patients were female and 86% were Caucasian. Patients treated with KALBITOR were between the ages of 10 and 78 years.

Overall, the most common adverse reactions in 255 patients with HAE were headache (16%), nausea (13%), fatigue (12%), diarrhea (11%), upper respiratory tract infection (8%), injection site reactions (7%), nasopharyngitis (6%), vomiting (6%), pruritus (5%), upper abdominal pain (5%), and pyrexia (5%).

Anaphylaxis was reported in 4% of patients with HAE. Injection site reactions were characterized by local pruritus, erythema, pain, irritation, urticaria, and/or bruising.

The incidence of adverse reactions below is based upon 2 placebo-controlled, clinical trials (EDEMA3® and EDEMA4) in a total of 143 unique patients with HAE. Patients were treated with KALBITOR 30 mg subcutaneous or placebo. Patients were permitted to participate sequentially in both placebo-controlled trials; safety data collected during exposure to KALBITOR was attributed to treatment with KALBITOR, and safety data collected during exposure to placebo was attributed to treatment with placebo. Table 1 shows adverse reactions occurring in ≥3% of KALBITOR-treated patients that also occurred at a higher rate than in the placebo-treated patients in the two controlled trials (EDEMA3 and EDEMA4) of the 30 mg subcutaneous dose.

Table 1: Adverse Reactions Occurring at ≥3% and Higher than Placebo in 2 Placebo Controlled Clinical Trials in Patients with HAE Treated with KALBITOR
 | KALBITOR N=100 | Placebo N=81
Adverse Reactions | n (%) [Patients experiencing more than 1 event with the same preferred term are counted only once for that preferred term.] | n (%)
Headache | 8 (8%) | 6 (7%)
Nausea | 5 (5%) | 1 (1%)
Diarrhea | 4 (4%) | 3 (4%)
Pyrexia | 4 (4%) | 0
Injection site reactions | 3 (3%) | 1 (1%)
Nasopharyngitis | 3 (3%) | 0

Some patients in EDEMA3 and EDEMA4 received a second, open-label 30 mg subcutaneous dose of KALBITOR within 24 hours following the initial dose. Adverse reactions reported by these patients who received the additional 30 mg subcutaneous dose of KALBITOR were consistent with those reported in the patients receiving a single dose.

6.2 Immunogenicity

In the KALBITOR HAE program, patients developed antibodies to KALBITOR. Rates of seroconversion increased with exposure to KALBITOR over time. Overall, 20.2% of patients seroconverted to anti-ecallantide antibodies. Neutralizing antibodies to ecallantide were determined in vitro to be present in 8.8% of patients and were not associated with loss of efficacy.

Anti-ecallantide IgE antibodies were detected at a rate of 4.7% for tested patients, and anti-P. pastoris IgE antibodies were also detected at a rate of 20.2%. Patients who seroconvert may be at a higher risk of a hypersensitivity reaction. The long-term effects of antibodies to KALBITOR are not known.

The test results for the ecallantide program were determined using one of two assay formats: ELISA and bridging electrochemiluminescence (ECL). As with all therapeutic proteins, there is a potential for immunogenicity with the use of KALBITOR. The incidence of antibody formation is highly dependent on the sensitivity and specificity of the assay. Additionally, the observed incidence of antibody (including neutralizing antibody) positivity in an assay may be influenced by several factors, including assay methodology, sample handling, timing of sample collection, concomitant medications, and underlying disease. For these reasons, comparison of the incidence of antibodies to KALBITOR with the incidence of antibodies to other products may be misleading.

6.3 Postmarketing Experience

Similar adverse reactions have been observed postmarketing as described for clinical trial experience. Because these events are reported voluntarily from a population of uncertain size, it is not always possible to reliably estimate frequency or to establish a causal relationship with drug exposure.

7 DRUG INTERACTIONS

No formal drug interactions studies were performed. No in vitro metabolism studies were performed.

8 USE IN SPECIFIC POPULATIONS

8.1 Pregnancy

Risk Summary

The available data from the pharmacovigilance database for KALBITOR have not identified a drug-associated risk of major birth defects, miscarriage or adverse maternal or fetal outcomes. In an animal reproduction study, increased early fetal deaths resulting in decreased live fetuses were observed in rats following treatment during the period of organogenesis at an intravenous dose approximately 1.6 times the maximum recommended human dose (MRHD) in the presence of maternal toxicity. There were no effects on embryofetal survival or structural abnormalities in rats and rabbits following treatment during the period of organogenesis with intravenous doses up to approximately 1.1 and 6 times the MRHD, respectively, or rats treated with subcutaneous doses up to 2.4 times the MRHD. In a pre- and post-natal development study with rats, there were no effects on pup survival and development with subcutaneous doses up to approximately 2.7 times the MRHD.

The estimated background risk of major birth defects and miscarriage for the indicated population is unknown. All pregnancies have a background risk of birth defect, loss, or other adverse outcomes. In the U.S. general population, the estimated background risk of major birth defects and miscarriage in clinically recognized pregnancies is 2% to 4% and 15% to 20%, respectively.

Data

Animal Data

In an embryofetal development study with rats, ecallantide administered by the intravenous route during the period of organogenesis from gestation days 7 to 17 at a dose approximately 1.6 times the MRHD (on a mg/m^2 basis at a maternal intravenous dose of 15 mg/kg/day) caused increased numbers of early resorptions and percentages of resorbed conceptuses per litter resulting in decreased numbers of live fetuses in the presence of mild maternal toxicity. No effects on embryofetal survival or structural abnormalities were observed in rats with intravenous doses up to approximately 1.1 times the MRHD (on a mg/m^2 basis with maternal intravenous dose of 10 mg/kg/day). In an embryofetal development study with rats, ecallantide administered by the subcutaneous route during the period of organogenesis from gestation days 7 to 17 at doses up to approximately 2.4 times the MRHD (on an AUC basis with maternal subcutaneous doses up to 20 mg/kg/day) had no effects on embryofetal survival or structural abnormalities. In an embryofetal development study with rabbits, ecallantide administered by the intravenous route during the period of organogenesis from gestation days 7 to 19 at doses up to approximately 6 times the MRHD (on an AUC basis with maternal intravenous doses up to 5 mg/kg/day in rabbits) had no effects on embryofetal survival or structural abnormalities.

In a pre- and post-natal development study with rats, ecallantide administered by the subcutaneous route from gestation day 7 through lactation day 20 at doses up to approximately 2.7 times the MRHD (on a mg/m^2 basis with maternal subcutaneous doses up to 25 mg/kg/day) had no effects on pup survival and behavioral or physical development.

8.2 Lactation

Risk Summary

There are no data on the presence of ecallantide in human milk, the effects on the breastfed infant, or the effects on milk production. The developmental and health benefits of breastfeeding should be considered along with the mother's clinical need for KALBITOR and any potential adverse effects on the breastfed child from KALBITOR or from the underlying maternal condition.

8.4 Pediatric Use

The safety and effectiveness of KALBITOR have been established in patients 12 to 17 years of age. The efficacy of KALBITOR in the 12-15 year age group is extrapolated from efficacy in patients 16 years of age and older with support from population pharmacokinetic analyses showing similar drug exposure levels in adults and adolescents [see Clinical Pharmacology (12.3) and Clinical Studies (14)]. The safety profile observed in pediatric patients 12-17 years of age was similar to the adverse reactions observed in the overall clinical trial population [see Adverse Reactions (6.1)].

Safety and effectiveness of KALBITOR in patients less than 12 years of age have not been established.

8.5 Geriatric Use

Clinical trials of KALBITOR did not include sufficient numbers of subjects aged 65 and over to determine whether they respond differently from younger subjects. In general, dose selection for an elderly patient should be cautious, usually starting at the low end of the dosing range, reflecting the greater frequency of decreased hepatic, renal, or cardiac function, and of concomitant disease or other drug therapy.

10 OVERDOSAGE

There have been no reports of overdose with KALBITOR. HAE patients have received single doses up to 90 mg intravenously without evidence of dose-related toxicity.

11 DESCRIPTION

KALBITOR (ecallantide) is a human plasma kallikrein inhibitor for injection for subcutaneous use. Ecallantide is a 60-amino-acid protein produced in Pichia pastoris yeast cells by recombinant DNA technology.

KALBITOR is a clear and colorless, sterile, and nonpyrogenic solution. Each vial contains 10 mg ecallantide as the active ingredient, and the following inactive ingredients: 0.76 mg disodium hydrogen orthophosphate (dihydrate), 0.2 mg monopotassium phosphate, 0.2 mg potassium chloride, and 8 mg sodium chloride in water for injection, USP. KALBITOR is preservative free, with a pH of approximately 7.0. A 30 mg dose is supplied as 3 vials each containing 1 mL of 10 mg/mL KALBITOR. Vials are intended for single use.

12 CLINICAL PHARMACOLOGY

12.1 Mechanism of Action

Hereditary angioedema (HAE) is a rare genetic disorder caused by mutations to C1-esterase-inhibitor (C1-INH) located on Chromosome 11q and inherited as an autosomal dominant trait. HAE is characterized by low levels of C1-INH activity and low levels of C4. C1-INH functions to regulate the activation of the complement and intrinsic coagulation (contact system pathway) and is a major endogenous inhibitor of plasma kallikrein. The kallikrein-kinin system is a complex proteolytic cascade involved in the initiation of both inflammatory and coagulation pathways. One critical aspect of this pathway is the conversion of High Molecular Weight (HMW) kininogen to bradykinin by the protease plasma kallikrein. In HAE, normal regulation of plasma kallikrein activity and the classical complement cascade is therefore not present. During attacks, unregulated activity of plasma kallikrein results in excessive bradykinin generation. Bradykinin is a vasodilator which is thought by some to be responsible for the characteristic HAE symptoms of localized swelling, inflammation, and pain.

KALBITOR is a potent (Ki = 25 pM), selective, reversible inhibitor of plasma kallikrein. KALBITOR binds to plasma kallikrein and blocks its binding site, inhibiting the conversion of HMW kininogen to bradykinin. By directly inhibiting plasma kallikrein, KALBITOR reduces the conversion of HMW kininogen to bradykinin and thereby treats symptoms of the disease during acute episodic attacks of HAE.

12.2 Pharmacodynamics

No exposure-response relationships for KALBITOR to components of the complement or kallikrein-kinin pathways have been established.

The effect of KALBITOR on activated partial thromboplastin time (aPTT) was measured because of potential effect on the intrinsic coagulation pathway. Prolongation of aPTT has been observed following intravenous dosing of KALBITOR at doses ≥20 mg/m^2. At 80 mg administered intravenously in healthy subjects, aPTT values were prolonged approximately two-fold over baseline values and returned to normal by 4 hours post-dose.

For patients taking KALBITOR, no significant QT prolongation has been seen. In a randomized, placebo-controlled trial (EDEMA4) studying the 30 mg subcutaneous dose versus placebo, 12-lead ECGs were obtained at baseline, 2 hours and 4 hours post-dose (covering the time of expected Cmax), and at follow-up (day 7). ECGs were evaluated for PR interval, QRS complex, and QTc interval. KALBITOR had no significant effect on the QTc interval, heart rate, or any other components of the ECG.

12.3 Pharmacokinetics

Following the administration of a single 30 mg subcutaneous dose of KALBITOR to healthy subjects, a mean (± standard deviation) maximum plasma concentration of 586 ± 106 ng/mL was observed approximately 2 to 3 hours post-dose. The mean area under the concentration-time curve was 3017 ± 402 ng*hr/mL. Following administration, plasma concentration declined with a mean elimination half-life of 2.0 ± 0.5 hours. Plasma clearance was 153 ± 20 mL/min and the volume of distribution was 26.4 ± 7.8 L. Based on a population pharmacokinetic analysis, body weight, age, and gender were not found to affect KALBITOR exposure significantly. Ecallantide is a small protein (7054 Da) and renal elimination in the urine of treated subjects has been demonstrated.

No pharmacokinetic data are available in patients or subjects with hepatic or renal impairment.

13 NONCLINICAL TOXICOLOGY

13.1 Carcinogenesis, Mutagenesis, Impairment of Fertility

A two-year study was conducted in rats to assess the carcinogenic potential of KALBITOR. No evidence of tumorigenicity was observed in rats at ecallantide doses up to 10 mg/kg administered subcutaneously every three days (approximately 2-fold greater than the MRHD on an AUC basis).

KALBITOR had no effects on fertility and reproductive performance in rats at maternal subcutaneous doses up to 25 mg/kg/day (approximately 2.7 times the MRHD on a mg/m^2 basis).

14 CLINICAL STUDIES

The safety and efficacy of KALBITOR to treat acute attacks of hereditary angioedema in adolescents and adults were evaluated in 2 randomized, double-blind, placebo-controlled trials (EDEMA4 and EDEMA3) in 168 patients with HAE. Patients having an attack of hereditary angioedema, at any anatomic location, with at least 1 moderate or severe symptom, were treated with 30 mg subcutaneous KALBITOR or placebo. Because patients could participate in both trials, a total of 143 unique patients participated. Of the 143 patients, 94 were female, 123 were Caucasian, and the mean age was 36 years (range 11-77). There were 64 patients with abdominal attacks, 55 with peripheral attacks, and 24 with laryngeal attacks.

In both trials, the effects of KALBITOR were evaluated using the Mean Symptom Complex Severity (MSCS) score and the Treatment Outcome Score (TOS). These endpoints evaluated attack severity (MSCS) and patient response to treatment (TOS) for an acute HAE attack.

MSCS score is a point-in-time measure of symptom severity. At baseline, and post-dosing at 4 hours and 24 hours, patients rated the severity of each affected symptom on a categorical scale (0 = normal, 1 = mild, 2 = moderate, 3 = severe). Patient-reported severity was based on each patient's assessment of symptom impact on their ability to perform routine activities. Ratings were averaged to obtain the MSCS score. The endpoint was reported as the change in MSCS score from baseline. A decrease in MSCS score reflected an improvement in symptom severity; the maximum possible change toward improvement was -3.

TOS is a measure of symptom response to treatment. At 4 hours and 24 hours post-dosing, patient assessment of response for each anatomic site of attack involvement was recorded on a categorical scale (significant improvement [100], improvement [50], same [0], worsening [-50], significant worsening [-100]). The response at each anatomic site was weighted by baseline severity and then the weighted scores across all involved sites were averaged to calculate the TOS. A TOS value >0 reflected an improvement in symptoms from baseline. The maximum possible score was +100.

EDEMA4

EDEMA4 was a randomized, double-blind, placebo-controlled trial in which 96 patients were randomized 1:1 to receive KALBITOR 30 mg subcutaneous or placebo for acute attacks of HAE. The primary endpoint was the change from baseline in MSCS score at 4 hours, and the TOS at 4 hours was a key secondary endpoint. Patients treated with KALBITOR demonstrated a greater decrease from baseline in the MSCS than placebo and a greater TOS than patients with placebo and the results were statistically significant (Table 2). At 24 hours, patients treated with KALBITOR also demonstrated a greater decrease from baseline in the MSCS than placebo (-1.5 vs. -1.1; p = 0.04) and a greater TOS (89 vs. 55, p = 0.03).

Table 2: Change in MSCS Score and TOS at 4 Hours
 | EDEMA4 |  |  | EDEMA3
 | KALBITOR (N=48) |  | Placebo (N=48) | KALBITOR (N=36) |  | Placebo (N=36)
Change in MSCS Score at 4 Hours
n | 47 |  | 42 | 34 |  | 35
Mean | -0.8 |  | -0.4 | -1.1 |  | -0.6
95% CI | -1.0, -0.6 |  | -0.6, -0.1 | -1.4, -0.8 |  | -0.8, -0.4
P-value |  | 0.010 |  |  | 0.041
TOS at 4 Hours
n | 47 |  | 42 | 34 |  | 35
Mean | 53 |  | 8 | 63 |  | 36
95% CI | 39, 68 |  | -12, 28 | 49, 76 |  | 17, 54
P-value |  | 0.003 |  |  | 0.045
MSCS: Mean Symptom Complex Severity
TOS: Treatment Outcome Score
CI: confidence interval

More patients in the placebo group (24/48, 50%) required medical intervention to treat unresolved symptoms within 24 hours compared to the KALBITOR-treated group (16/48, 33%).

Some patients reported improvement following a second 30 mg subcutaneous dose of KALBITOR, administered within 24 hours following the initial dose for symptom persistence or relapse, but efficacy was not systematically assessed for the second dose.

EDEMA3

EDEMA3 was a randomized, double-blind, placebo-controlled trial in which 72 patients were randomized 1:1 to receive KALBITOR or placebo for acute attacks of HAE. EDEMA3 was similar in design to EDEMA4 with the exception of the order of the prespecified efficacy endpoints. In EDEMA3, the primary endpoint was the TOS at 4 hours, and the key secondary efficacy endpoint was the change from baseline in MSCS at 4 hours. As in EDEMA4, patients treated with KALBITOR demonstrated a greater decrease from baseline in the MSCS than placebo and a greater TOS than patients treated with placebo and the results were statistically significant (Table 2).

In addition, more patients in the placebo group (13/36, 36%) required medical intervention to treat unresolved symptoms within 24 hours compared to the KALBITOR-treated group (5/36, 14%).

16 HOW SUPPLIED/STORAGE AND HANDLING

KALBITOR (ecallantide) is supplied as three 10 mg/mL single-dose vials packaged in a carton. Each vial contains 10 mg of ecallantide. Each vial contains a slight overfill.

- NDC (47783-101-01): 3 single-dose vials in 1 carton

STORAGE AND HANDLING

KALBITOR should be kept refrigerated (2°C to 8°C/36°F to 46°F). Vials removed from refrigeration should be stored below 86°F/30°C and used within 14 days or returned to refrigeration until use.

Protect vials from light until use.

Do not use beyond the expiration date.

17 PATIENT COUNSELING INFORMATION

See FDA-approved patient labeling (Medication Guide)

- Advise patients that KALBITOR may cause anaphylaxis and other hypersensitivity reactions. Advise patients that KALBITOR should be administered by a healthcare professional with appropriate medical support to manage anaphylaxis and hereditary angioedema. Instruct patients who have known clinical hypersensitivity to KALBITOR not to receive additional doses of KALBITOR. [see Boxed Warning, Contraindications (4), and Warnings and Precautions (5.1)]
- Advise patients to consult the Medication Guide for additional information regarding the risk of anaphylaxis and other hypersensitivity reactions.

For more information, visit www.kalbitor.com or call 1-877-TAKEDA-7 (1-877-825-3327).

Manufactured by:
Takeda Pharmaceuticals U.S.A., Inc.
Cambridge, MA 02142

U.S. License No. 1898

KALBITOR and the KALBITOR Logo are registered trademarks of Dyax Corp.

Takeda and are registered trademarks of Takeda Pharmaceutical Company Limited.

© 2025 Takeda Pharmaceuticals U.S.A., Inc. All rights reserved.

Medication Guide

KALBITOR® (KAL-bi-tor)
(ecallantide)

Read this Medication Guide before you start receiving KALBITOR and before each treatment. There may be new information. This Medication Guide does not take the place of talking to your doctor about your medical condition or your treatment.

What is the most important information that I should know about KALBITOR?

Serious allergic reactions may happen in some people who receive KALBITOR. These allergic reactions can be life-threatening and usually happen within 1 hour after receiving KALBITOR.

- KALBITOR should be given to you by a doctor or nurse in a healthcare setting where serious allergic reactions and hereditary angioedema (HAE) can be treated.
- Symptoms of a serious allergic reaction to KALBITOR can be similar to the symptoms of HAE, the condition that you are being treated for. Your doctor or nurse should watch you for any signs of a serious allergic reaction after treatment with KALBITOR.
- Tell your doctor or nurse right away if you have any of these symptoms of a serious allergic reaction during or after treatment with KALBITOR:
  - wheezing, shortness of breath, cough, chest tightness, or trouble breathing
  - dizziness, fainting, fast or weak heartbeat, or feeling nervous
  - reddening of the face, itching, hives, or feeling warm
  - swelling of the throat or tongue, throat tightness, hoarse voice, or trouble swallowing
  - runny nose, nasal congestion, or sneezing

What is KALBITOR?

KALBITOR is a prescription medicine used to treat sudden attacks of hereditary angioedema (HAE) in people 12 years of age and older.

KALBITOR is not a cure for HAE.

It is not known if KALBITOR is safe and effective in children under 12 years of age.

Who should not receive KALBITOR?

Do not receive KALBITOR if you are allergic to KALBITOR.

What should I tell my doctor before I receive KALBITOR?

Before receiving KALBITOR, tell your doctor if you:

- have ever had an allergic reaction to KALBITOR. See "Who should not receive KALBITOR?"
- are pregnant or plan to become pregnant. It is not known if KALBITOR will harm your unborn baby.
- are breast-feeding or plan to breast-feed. It is not known if KALBITOR passes into your breast milk.

Tell your doctor about all the medicines you take, including prescription and over-the-counter medicines, vitamins, and herbal supplements.

Know the medicines you take. Keep a list of them to show to your doctor and pharmacist when you get a new medicine.

How will I receive KALBITOR?

For each dose, you will receive 3 injections just under the skin (subcutaneous or SC injections) of your abdomen, thigh, or upper arm.

What are the possible side effects?

KALBITOR can cause serious allergic reactions. See "What is the most important information I should know about KALBITOR?"

Common side effects of KALBITOR include:

- headache
- nausea
- diarrhea
- fever
- injection site reactions, such as redness, rash, swelling, itching, or bruising
- stuffy nose

Call your doctor for advice about side effects. You may report side effects to FDA at 1-800-FDA-1088.

General information about KALBITOR

Medicines are sometimes prescribed for purposes other than those listed in a Medication Guide. This Medication Guide gives you the most important information about KALBITOR. If you would like more information, talk with your doctor. You can ask your pharmacist or doctor for information about KALBITOR that is written for health professionals.

What are the ingredients of KALBITOR?

Active Ingredient: ecallantide

Inactive ingredients: disodium hydrogen orthophosphate (dihydrate), monopotassium phosphate, potassium chloride, sodium chloride in water for injection.

This Medication Guide has been approved by the U.S. Food and Drug Administration.

For more information, visit www.kalbitor.com or call 1-877-TAKEDA-7 (1-877-825-3327).

Manufactured by:
Takeda Pharmaceuticals U.S.A., Inc.
Cambridge, MA 02142

U.S. License No. 1898

KALBITOR and the KALBITOR Logo are registered trademarks of Dyax Corp.

Takeda and are registered trademarks of Takeda Pharmaceutical Company Limited.

© 2025 Takeda Pharmaceuticals U.S.A., Inc. All rights reserved.

Revised: 6/2025

PRINCIPAL DISPLAY PANEL - 10 mg/mL Vial Carton

ATTENTION: Dispense the enclosed
Medication Guide to each patient.
NDC# 47783-101-01

KALBITOR®

ecallantide

10 mg/mL
Injection
For Subcutaneous Use Only
Single-Dose ;Discard Unused Portion
Net Quantity: 3 Vials

Rx Only

PRINCIPAL DISPLAY PANEL - 10 mg/mL Vial Bottle

NDC 47783-101-01

KALBITOR®

ecallantide

10 mg/mL
Single-Dose; Discard Unused Portion
Rx Only. For Subcutaneous Use Only.
Takeda Pharmaceuticals U.S.A., Inc.